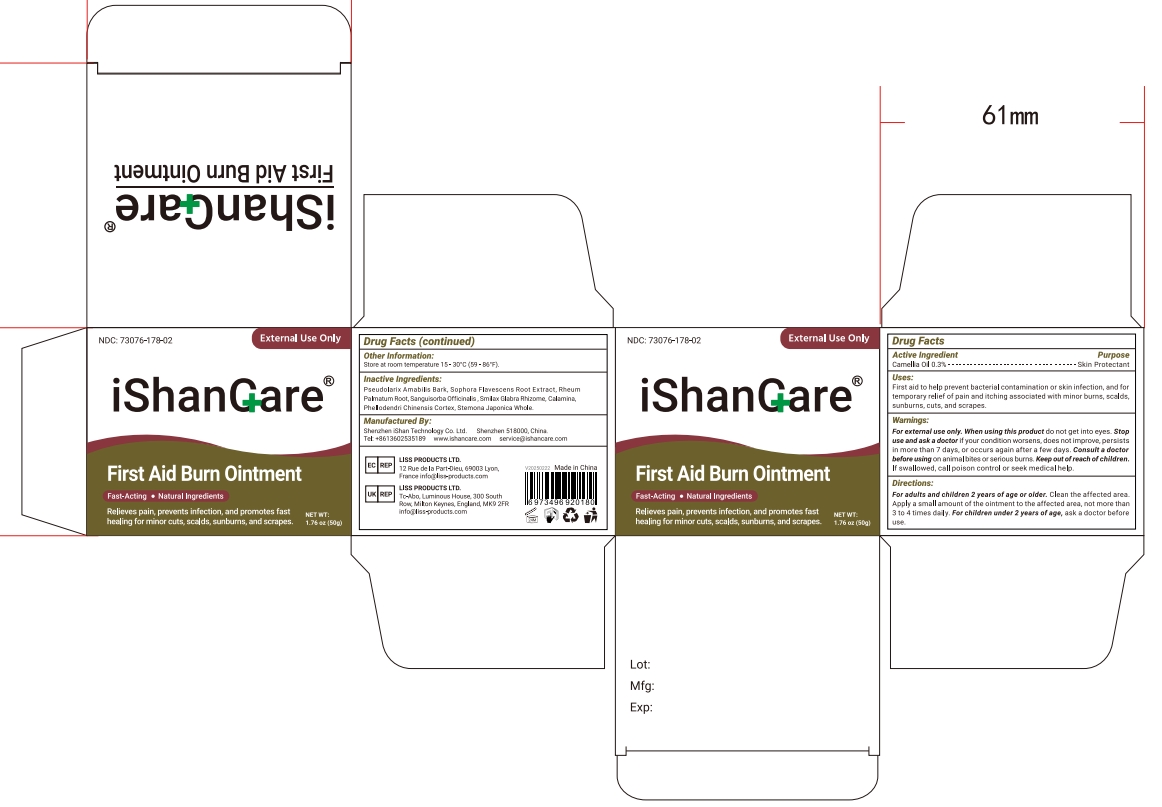 DRUG LABEL: iShanCare
NDC: 73076-178 | Form: OINTMENT
Manufacturer: Shenzhen Ishan Technology Co., Ltd
Category: homeopathic | Type: HUMAN OTC DRUG LABEL
Date: 20260212

ACTIVE INGREDIENTS: CAMELLIA OIL 0.3 g/100 g
INACTIVE INGREDIENTS: PSEUDOLARIX AMABILIS BARK; SOPHORA FLAVESCENS ROOT; RHEUM PALMATUM ROOT; SANGUISORBA OFFICINALIS ROOT; SMILAX GLABRA TUBER; ZINC OXIDE; FERRIC OXIDE RED; PHELLODENDRINE; STEMONA JAPONICA WHOLE

Active ingredient

Camellia Oil 0.3%

Inactive ingredient

Pseudolarix Amabilis Bark, Sophora Flavescens Root Extract, RheumPalmatum Root, Sanguisorba Officinalis , Smilax Glabra Rhizome, Calamina,Phellodendri Chinensis Cortex, Stemona Japonica Whole.

Keep out of reach of children.

if swallowed, call poison control or seek medical help.

Stop use and ask a doctor if

pain worsens or persists, or if youexperience any of these symptoms: burning, itching, rash, or other changes in theskin where the product was placed.

USES

First aid to help prevent bacterial contamination or skin infection, and fortemporary relief of pain and itching associated with minor burns, scaldssunburns, cuts, and scrapes.

Other information

Store in a cool, dry place.
This is not a toy and should be kept out of reach of young children.

Discard the product if the packaging has been opened. Do not use.

Directions

For adults and children 2 years ofage or older. Clean the affected area.Apply a small amount of the ointment to the affected area, not more than3 to 4 times daily. For children under 2 years ofage, ask a doctor before use.

Dosage & administration

Apply not more than 3 to 4 times

When using this product

Do not wear this product directly on skin.

Be aware of low-temperature burns.

Warning

For external use only. When using this product do not get into eyes. Stopuse and ask a doctor if your condition worsens, does not improve, persistsin more than 7 days, or occurs again after a few days. Consult a doctorbefore using on animal bites or serious burns. Keep out ofreach of childrenf swallowed, call poison control or seek medical help.

RECENT MAJOR CHANGES

no